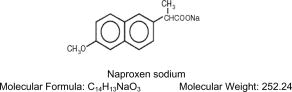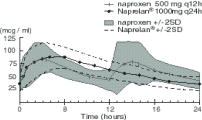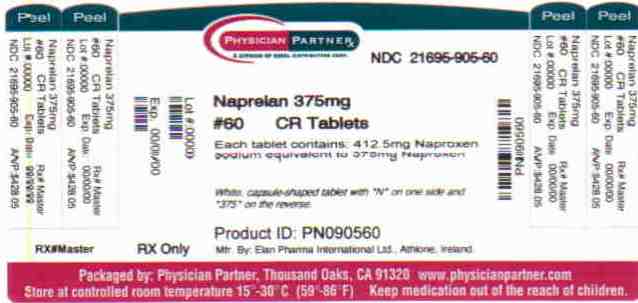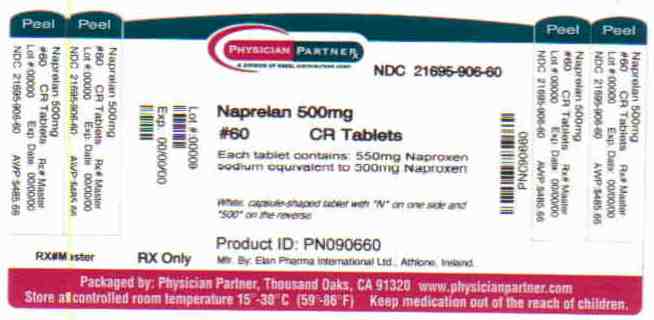 DRUG LABEL: NAPRELAN
NDC: 21695-905 | Form: TABLET, FILM COATED, EXTENDED RELEASE
Manufacturer: Rebel Distributors Corp
Category: prescription | Type: HUMAN PRESCRIPTION DRUG LABEL
Date: 20101229

ACTIVE INGREDIENTS: naproxen sodium 375 mg/1 1
INACTIVE INGREDIENTS: anhydrous citric acid; crospovidone; magnesium stearate; cellulose, microcrystalline; povidone; talc; HYPROMELLOSES; polyethylene glycol; titanium dioxide

NAPRELAN® (naproxen sodium)
CONTROLLED-RELEASE TABLETS

Equivalent to 375mg, 500mg and 750mg naproxen
NAPRELAN® Controlled-Release Tablets, 375mg, 500mg and 750mg

BOXED WARNING

Cardiovascular Risk

- NSAIDs may cause an increased risk of serious cardiovascular thrombotic events, myocardial infarction, and stroke, which can be fatal. This risk may increase with duration of use. Patients with cardiovascular disease or risk factors for cardiovascular disease may be at greater risk. (See WARNINGS).
- Naproxen as NAPRELAN® is contraindicated for the treatment of peri-operative pain in the setting of coronary artery bypass graft (CABG) surgery (SeeWARNINGS).

Gastrointestinal Risk

- NSAIDs cause an increased risk of serious gastrointestinal adverse events including bleeding, ulceration, and perforation of the stomach or intestines, which can be fatal. These events can occur at any time during use and without warning symptoms. Elderly people are at greater risk for serous gastrointestinal events. (SeeWARNINGS).

DESCRIPTION

NAPRELAN®* Tablets contain naproxen sodium, a member of the arylacetic acid group of nonsteroidal anti-inflammatory drugs (NSAIDs). NAPRELAN® Tablets use the proprietary IPDAS®** (Intestinal Protective Drug Absorption System) technology. It is a rapidly disintegrating tablet system combining an immediate release component and a sustained release component of microparticles that are widely dispersed, allowing absorption of the active ingredient throughout the gastrointestinal (GI) tract, maintaining blood levels over 24 hours. The chemical name for naproxen sodium is 2-naphthaleneacetic acid, 6-methoxy-a-methyl-sodium salt, (S)- with the following structural formula:

Naproxen sodium is an odorless crystalline powder, white to creamy in color. It is soluble in methanol and water. NAPRELAN® Tablets contain 412.5 mg, 550 mg, or 825 mg of naproxen sodium, equivalent to 375 mg, 500 mg, and 750 mg of naproxen and 37.5, mg 50 mg, and 75 mg sodium respectively. Each NAPRELAN® Tablet also contains the following inactive ingredients: ammoniomethacrylate copolymer Type A, ammoniomethacrylate copolymer Type B, citric acid, crospovidone, magnesium stearate, methacrylic acid copolymer Type A, microcrystalline cellulose, povidone, and talc. The tablet coating contains hydroxypropyl methylcellulose, polyethylene glycol, and titanium dioxide.

CLINICAL PHARMACOLOGY

Naproxen is a nonsteroidal anti-inflammatory drug (NSAID), with analgesic and antipyretic properties. As with other NSAIDs, its mode of action is not fully understood; however, its ability to inhibit prostaglandin synthesis may be involved in the anti-inflammatory effect.

PHARMACOKINETICS

Although naproxen itself is well absorbed, the sodium salt form is more rapidly absorbed, resulting in higher peak plasma levels for a given dose. Approximately 30% of the total naproxen sodium dose in NAPRELAN® Tablets is present in the dosage form as an immediate release component. The remaining naproxen sodium is coated as microparticles to provide sustained release properties. After oral administration, plasma levels of naproxen are detected within 30 minutes of dosing, with peak plasma levels occurring approximately 5 hours after dosing. The observed terminal elimination half-life of naproxen from both immediate release naproxen sodium and NAPRELAN® Tablets is approximately 15 hours. Steady state levels of naproxen are achieved in 3 days and the degree of naproxen accumulation in the blood is consistent with this.

Pharmacokinetic Parameters at Steady State Day 5 (Mean of 24 Subjects)
 | Parameter (units) | naproxen 500 mg Q12h/5 days (1000 mg) |  |  | NAPRELAN® 2 x 500 mg tablets (1000 mg) Q24h/5 days
 |  | Mean | SD | Range | Mean | SD | Range
 | AUC 0-24 (mcgxh/mL) | 1446 | 168 | 1167 - 1858 | 1448 | 145 | 1173 - 1774
 | Cmax (mcg/mL) | 95 | 13 | 71 - 117 | 94 | 13 | 74 - 127
 | Cavg (mcg/mL) | 60 | 7 | 49 - 77 | 60 | 6 | 49 - 74
 | Cmin (mcg/mL) | 36 | 9 | 13 - 51 | 33 | 7 | 23 - 48
 | Tmax (hrs) | 3 | 1 | 1 - 4 | 5 | 2 | 2-10

Absorption

Naproxen itself is rapidly and completely absorbed from the GI tract with an in vivo bioavailability of 95%. Based on the pharmacokinetic profile, the absorption phase of NAPRELAN® Tablets occurs in the first 4-6 hours after administration. This coincides with disintegration of the tablet in the stomach, the transit of the sustained release microparticles through the small intestine and into the proximal large intestine. An in vivo imaging study has been performed in healthy volunteers that confirms rapid disintegration of the tablet matrix and dispersion of the microparticles.

The absorption rate from the sustained release particulate component of NAPRELAN® Tablets is slower than that for conventional naproxen sodium tablets. It is this prolongation of drug absorption processes that maintains plasma levels and allows for once daily dosing.

Food Effects

No significant food effects were observed when twenty-four subjects were given a single dose of NAPRELAN® Tablets 500 mg either after an overnight fast or 30 minutes after a meal. In common with conventional naproxen and naproxen sodium formulations, food causes a slight decrease in the rate of naproxen absorption following NAPRELAN® Tablets administration.

Distribution

Naproxen has a volume of distribution of 0.16 L/kg. At therapeutic levels, naproxen is greater than 99% albumin-bound. At doses of naproxen greater than 500 mg/day, there is a less than proportional increase in plasma levels due to an increase in clearance caused by saturation of plasma protein binding at higher doses. However the concentration of unbound naproxen continues to increase proportionally to dose. NAPRELAN® Tablets exhibit similar dose proportional characteristics.

Metabolism

Naproxen is extensively metabolized to 6-0-desmethyl naproxen and both parent and metabolites do not induce metabolizing enzymes.

Elimination

The elimination half-life of NAPRELAN® Tablets and conventional naproxen is approximately 15 hours. Steady state conditions are attained after 2-3 doses of NAPRELAN® Tablets. Most of the drug is excreted in the urine, primarily as unchanged naproxen (less than 1%), 6-0-desmethyl naproxen (less than 1%) and their glucuronide or other conjugates (66-92%). A small amount (<5%) of the drug is excreted in the feces. The rate of excretion has been found to coincide closely with the rate of clearance from the plasma. In patients with renal failure, metabolites may accumulate.

Special Populations

Pediatric Use

No pediatric studies have been performed with NAPRELAN® Tablets, thus safety of NAPRELAN® Tablets in pediatric populations has not been established.

Renal Insufficiency

Naproxen pharmacokinetics have not been determined in subjects with renal insufficiency. Given that naproxen is metabolized and conjugates are primarily excreted by the kidneys, the potential exists for naproxen metabolites to accumulate in the presence of renal insufficiency. Elimination of naproxen is decreased in patients with severe renal impairment. Naproxen-containing products are not recommended for use in patients with moderate to severe and severe renal impairment (creatinine clearance <30mL/min)(see WARNINGS – Renal Effects).

CLINICAL STUDIES

RHEUMATOID ARTHRITIS

The use of NAPRELAN® Tablets for the management of the signs and symptoms of rheumatoid arthritis was assessed in a 12 week double-blind, randomized, placebo and active-controlled study in 348 patients. Two NAPRELAN® 500 mg tablets (1000 mg) once daily and naproxen 500 mg tablets twice daily (1000 mg) were more effective than placebo. Clinical effectiveness was demonstrated at one week and continued for the duration of the study.

OSTEOARTHRITIS

The use of NAPRELAN® Tablets for the management of the signs and symptoms of osteoarthritis of the knee was assessed in a 12 week double-blind, placebo and active-controlled study in 347 patients. Two NAPRELAN® 500 mg tablets (1000 mg) once daily and naproxen 500 mg tablets twice daily (1000 mg) were more effective than placebo. Clinical effectiveness was demonstrated at one week and continued for the duration of the study.

ANALGESIA

The onset of the analgesic effect of NAPRELAN® Tablets was seen within 30 minutes in a pharmacokinetic/pharmacodynamic study of patients with pain following oral surgery. In controlled clinical trials, naproxen has been used in combination with gold, D-penicillamine, methotrexate and corticosteroids. Its use in combination with salicylate is not recommended because there is evidence that aspirin increases the rate of excretion of naproxen and data are inadequate to demonstrate that naproxen and aspirin produce greater improvement over that achieved with aspirin alone. In addition, as with other NSAIDs the combination may result in higher frequency of adverse events than demonstrated for either product alone.

SPECIAL STUDIES

In a double-blind randomized, parallel group study, 19 subjects received either two NAPRELAN® 500 mg tablets (1000 mg) once daily or naproxen 500 mg tablets (1000 mg) twice daily for 7 days. Mucosal biopsy scores and endoscopic scores were lower in the subjects who received NAPRELAN® Tablets. In another double-blind, randomized, crossover study, 23 subjects received two NAPRELAN® 500 mg tablets (1000 mg) once daily, naproxen 500 mg tablets (1000 mg) twice daily and aspirin 650 mg four times daily (2600 mg) for 7 days each. There were significantly fewer duodenal erosions seen with NAPRELAN® Tablets than with either naproxen or aspirin. There were significantly fewer gastric erosions with both NAPRELAN® Tablets and naproxen than with aspirin. The clinical significance of these findings is unknown.

INDICATIONS AND USAGE

Carefully consider the potential benefits and risks of NAPRELAN® Tablets and other treatment options before deciding to use NAPRELAN® Tablets. Use the lowest effective dose for the shortest duration consistent with individual patient treatment goals (see WARNINGS).

NAPRELAN® Tablets are indicated for the treatment of rheumatoid arthritis, osteoarthritis, ankylosing spondylitis, tendinitis, bursitis and acute gout. It is also indicated in the relief of mild to moderate pain and the treatment of primary dysmenorrhea.

CONTRAINDICATIONS

NAPRELAN® is contraindicated in patients with known hypersensitivity to naproxen.

NAPRELAN® should not be given to patients who have experienced asthma, urticaria, or allergic-type reactions after taking aspirin or other NSAIDs. Severe, rarely fatal, anaphylactic-like reactions to NSAIDs have been reported in such patients (see WARNINGS- Anaphylactoid Reactions, and PRECAUTIONS- Preexisting Asthma).

NAPRELAN® is contraindicated for the treatment of peri-operative pain in the setting of coronary artery bypass graft (CABG) surgery (see WARNINGS).

WARNINGS

CARDIOVASCULAR EFFECTS

Cardiovascular Thrombotic Events

Clinical trials of several COX-2 selective and nonselective NSAIDs of up to three years duration have shown an increased risk of serious cardiovascular (CV) thrombotic events, myocardial infarction, and stroke, which can be fatal. All NSAIDs, both COX-2 selective and nonselective, may have a similar risk. Patients with known CV disease or risk factors for CV disease may be at greater risk. To minimize the potential risk for an adverse CV event in patients treated with an NSAID, the lowest effective dose should be used for the shortest duration possible. Physicians and patients should remain alert for the development of such events, even in the absence of previous CV symptoms. Patients should be informed about the signs and/or symptoms of serious CV events and the steps to take if they occur.

There is no consistent evidence that concurrent use of aspirin mitigates the increased risk of serious CV thrombotic events associated with NSAID use. The concurrent use of aspirin and an NSAID does increase the risk of serious GI events (see GI Effects – Risk of Ulceration, Bleeding, and Perforation).

Two large, controlled, clinical trials of a COX-2 selective NSAID for the treatment of pain in the first 10-14 days following CABG surgery found an increased incidence of myocardial infarction and stroke (see CONTRAINDICATIONS).

Hypertension

NSAIDs, including NAPRELAN® can lead to onset of new hypertension or worsening of preexisting hypertension, either of which may contribute to the increased incidence of CV events. Patients taking thiazides or loop diuretics may have impaired response to these therapies when taking NSAIDs. NSAIDs, including NAPRELAN®, should be used with caution in patients with hypertension. Blood pressure (BP) should be monitored closely during the initiation of NSAID treatment and throughout the course of therapy.

Congestive Heart Failure and Edema

Fluid retention and edema have been observed in some patients taking NSAIDs. NAPRELAN® should be used with caution in patients with fluid retention or heart failure.

GASTROINTESTINAL EFFECTS - Risk of Ulceration, Bleeding, and Perforation

NSAIDs, including NAPRELAN®, can cause serious gastrointestinal (GI) adverse events including inflammation, bleeding, ulceration, and perforation of the stomach, small intestine, or large intestine, which can be fatal. These serious adverse events can occur at any time, with or without warning symptoms, in patients treated with NSAIDs. Only one in five patients who develop a serious upper GI adverse event on NSAID therapy is symptomatic. Upper GI ulcers, gross bleeding, or perforation caused by NSAIDs occur in approximately 1% of patients treated for 3-6 months, and in about 2-4% of patients treated for one year. These trends continue with longer duration of use, increasing the likelihood of developing a serious GI event at some time during the course of therapy. However, even short-term therapy is not without risk.

NSAIDs should be prescribed with extreme caution in those with a prior history of ulcer disease or gastrointestinal bleeding. Patients with a prior history of peptic ulcer disease and/or gastrointestinal bleeding who use NSAIDs have a greater than 10-fold increased risk for developing a GI bleed compared to patients with neither of these risk factors. Other factors that increase the risk for GI bleeding in patients treated with NSAIDs include concomitant use of oral corticosteroids or anticoagulants, longer duration of NSAID therapy, smoking, use of alcohol, older age, and poor general health status. Most spontaneous reports of fatal GI events are in elderly or debilitated patients and therefore, special care should be taken in treating this population.

To minimize the potential risk for an adverse GI event in patients treated with an NSAID, the lowest effective dose should be used for the shortest possible duration. Patients and physicians should remain alert for signs and symptoms of GI ulceration and bleeding during NSAID therapy and promptly initiate additional evaluation and treatment if a serious GI adverse event is suspected. This should include discontinuation of the NSAID until a serious GI adverse event is ruled out. For high risk patients, alternate therapies that do not involve NSAIDs should be considered.

RENAL EFFECTS

Long-term administration of NSAIDs has resulted in renal papillary necrosis and other renal injury. Renal toxicity has also been seen in patients in whom renal prostaglandins have a compensatory role in the maintenance of renal perfusion. In these patients, administration of a nonsteroidal anti-inflammatory drug may cause a dose-dependent reduction in prostaglandin formation and, secondarily, in renal blood flow, which may precipitate overt renal decompensation. Patients at greatest risk of this reaction are those with impaired renal function, heart failure, liver dysfunction, those taking diuretics and ACE inhibitors, and the elderly. Discontinuation of NSAID therapy is usually followed by recovery to the pretreatment state.

Advanced Renal Disease

No information is available from from controlled clinical studies regarding the use of NAPRELAN® in patients with advanced renal disease. Therefore, treatment with NAPRELAN® is not recommended in those patients with advanced renal disease. If NAPRELAN® therapy must be initiated, close monitoring of the patient's renal function is advisable.

ANAPHYLACTOID REACTIONS

As with other NSAIDs, anaphylactoid reactions may occur in patients without known prior exposure to NAPRELAN®. NAPRELAN® should not be given to patients with the aspirin triad. This symptom complex typically occurs in asthmatic patients who experience rhinitis with or without nasal polyps, or who exhibit severe, potentially fatal bronchospasm after taking aspirin or other NSAIDs (see CONTRAINDICATIONS and PRECAUTIONS- Preexisting Asthma). Emergency help should be sought in cases where an anaphylactoid reaction occurs.

SKIN REACTIONS

NSAIDs, including NAPRELAN®, can cause serious skin adverse events such as exfoliative dermatitis, Stevens-Johnson Syndrome (SJS), and toxic epidermal necrolysis (TEN), which can be fatal. These serious events may occur without warning. Patients should be informed about the signs and symptoms of serious skin manifestations and use of the drug should be discontinued at the first appearance of skin rash or any other sign of hypersensitivity.

PREGNANCY

In late pregnancy, as with other NSAIDs, NAPRELAN® should be avoided because it may cause premature closure of the ductus arteriosus.

PRECAUTIONS

General

NAPRELAN® cannot be expected to substitute for corticosteroids or to treat corticosteroid insufficiency. Abrupt discontinuation of corticosteroids may lead to disease exacerbation. Patients on prolonged corticosteroid therapy should have their therapy tapered slowly if a decision is made to discontinue corticosteroids. The pharmacological activity of NAPRELAN® in reducing fever and inflammation may diminish the utility of these diagnostic signs in detecting complications of presumed noninfectious, painful conditions.

Hepatic Effects

Borderline elevations of one or more liver tests may occur in up to 15% of patients taking NSAIDs including NAPRELAN®. These laboratory abnormalities may progress, may remain unchanged, or may be transient with continuing therapy. Notable elevations of ALT or AST (approximately three or more times the upper limit of normal) have been reported in approximately 1% of patients in clinical trials with NSAIDs. In addition, rare cases of severe hepatic reactions, including jaundice and fatal fulminant hepatitis, liver necrosis and hepatic failure, some of them with fatal outcomes have been reported.

A patient with symptoms and/or signs suggesting liver dysfunction, or in whom an abnormal liver test has occurred, should be evaluated for evidence of the development of a more severe hepatic reaction while on therapy with NAPRELAN®. If clinical signs and symptoms consistent with liver disease develop, or if systemic manifestations occur (e.g., eosinophilia, rash, etc.), NAPRELAN® should be discontinued.

Hematological Effects

Anemia is sometimes seen in patients receiving NSAIDs, including NAPRELAN®. This may be due to fluid retention, occult or gross GI blood loss, or an incompletely described effect upon erythropoiesis. Patients on long-term treatment with NSAIDs, including NAPRELAN®, should have their hemoglobin or hematocrit checked if they exhibit any signs or symptoms of anemia.

NSAIDs inhibit platelet aggregation and have been shown to prolong bleeding time in some patients. Unlike aspirin, their effect on platelet function is quantitatively less, of shorter duration, and reversible. Patients receiving NAPRELAN® who may be adversely affected by alterations in platelet function, such as those with coagulation disorders or patients receiving anticoagulants, should be carefully monitored.

Preexisting Asthma

Patients with asthma may have aspirin-sensitive asthma. The use of aspirin in patients with aspirin-sensitive asthma has been associated with severe bronchospasm which can be fatal. Since cross reactivity, including bronchospasm, between aspirin and other nonsteroidal anti-inflammatory drugs has been reported in such aspirin-sensitive patients, NAPRELAN® should not be administered to patients with this form of aspirin sensitivity and should be used with caution in patients with preexisting asthma.

INFORMATION FOR PATIENTS

Patients should be informed of the following information before initiating therapy with an NSAID and periodically during the course of ongoing therapy. Patients should also be encouraged to read the NSAID Medication Guide that accompanies each prescription dispensed.

1. NAPRELAN®, like other NSAIDs, may cause serious CV side effects, such as MI or stroke, which may result in hospitalization and even death. Although serious CV events can occur without warning symptoms, patients should be alert for the signs and symptoms of chest pan, shortness of breath, weakness, slurring of speech, and should ask for medical advice when observing any indicative sign or symptoms. Patients should be apprised of the importance of this follow-up (see WARNINGS, Cardiovascular Effects).
2. NAPRELAN®, like other NSAIDs, can cause GI discomfort and, rarely, serious GI side effects, such as ulcers and bleeding, which may result in hospitalization and even death. Although serious GI tract ulcerations and bleeding can occur without warning symptoms, patients should be alert for the signs and symptoms of ulcerations and bleeding, and should ask for medical advice when observing any indicative sign or symptoms including epigastric pain, dyspepsia, melena, and hematemesis. Patients should be apprised of the importance of this follow-up (see WARNINGS, Gastrointestinal Effects: Risk of Ulceration, Bleeding and Perforation).
3. NAPRELAN®, like other NSAIDs, can cause serious skin side effects such as exfoliative dermatitis, SJS, and TEN, which may result in hospitalization and even death. Although serious skin reactions may occur without warning, patients should be alert for the signs and symptoms of skin rash and blisters, fever, or other signs of hypersensitivity such as itching, and should ask for medical advice when observing any indicative signs or symptoms. Patients should be advised to stop the drug immediately if they develop any type of rash and contact their physicians as soon as possible.
4. Patients should promptly report signs or symptoms of unexplained weight gain or edema to their physicians.
5. Patients should be informed of the warning signs and symptoms of hepatotoxicity (e.g., nausea, fatigue, lethargy, pruritus, jaundice, right upper quadrant tenderness, and “flu-like” symptoms). If these occur, patients should be instructed to stop therapy and seek immediate medical therapy.
6. Patients should be informed of the signs of an anaphylactoid reaction (e.g., difficulty breathing, swelling of the face or throat). If these occur, patients should be instructed to seek immediate emergency help (see WARNINGS).
7. In late pregnancy, as with other NSAIDs, NAPRELAN® should be avoided because it may cause premature closure of the ductus arteriosus.

Laboratory Tests

Because serious GI tract ulcerations and bleeding can occur without warning symptoms, physicians should monitor for signs or symptoms of GI bleeding. Patients on long-term treatment with NSAIDs, should have their CBC and a chemistry profile checked periodically. If clinical signs and symptoms consistent with liver or renal disease develop, systemic manifestations occur (e.g., eosinophilia, rash, etc.) or if abnormal liver tests persist or worsen, NAPRELAN® should be discontinued.

DRUG INTERACTIONS

ACE-inhibitors

Reports suggest that NSAIDs may diminish the antihypertensive effect of ACE-inhibitors. This interaction should be given consideration in patients taking NSAIDs concomitantly with ACE-inhibitors.

Aspirin

When NAPRELAN® is administered with aspirin, its protein binding is reduced, although the clearance of free NAPRELAN® is not altered. The clinical significance of this interaction is not known; however, as with other NSAIDs, concomitant administration of naproxen and aspirin is not generally recommended because of the potential of increased adverse effects.

Diuretics

Clinical studies, as well as post-marketing observations, have shown that NAPRELAN® can reduce the natriuretic effect of furosemide and thiazides in some patients. This response has been attributed to inhibition of renal prostaglandin synthesis. During concomitant therapy with NSAIDs, the patient should be observed closely for signs of renal failure (see WARNINGS, Renal Effects), as well as to assure diuretic efficacy.

Lithium

NSAIDs have produced an elevation of plasma lithium levels and a reduction in renal lithium clearance. The mean minimum lithium concentration increased 15% and the renal clearance was decreased by approximately 20%. These effects have been attributed to inhibition of renal prostaglandin synthesis by the NSAID. Thus, when NSAIDs and lithium are administered concurrently, subjects should be observed carefully for signs of lithium toxicity.

Methotrexate

NSAIDs have been reported to competitively inhibit methotrexate accumulation in rabbit kidney slices. This may indicate that they could enhance the toxicity of methotrexate. Caution should be used when NSAIDs are administered concomitantly with methotrexate.

Warfarin

The effects of warfarin and NSAIDs on GI bleeding are synergistic, such that users of both drugs together have a risk of serious GI bleeding higher than users of either drug alone.

DRUG/LABORATORY TEST INTERACTIONS

Naproxen may decrease platelet aggregation and prolong bleeding time. This effect should be kept in mind when bleeding times are determined.

The administration of naproxen may result in increased urinary values for 17-ketogenic steroids because of an interaction between the drug and/or its metabolites with m-dinitrobenzene used in this assay. Although 17-hydroxy-corticosteroid measurements (Porter-Silber test) do not appear to be artificially altered, it is suggested that therapy with naproxen be temporarily discontinued 72 hours before adrenal function tests are performed if the Porter-Silber test is to be used.

Naproxen may interfere with some urinary assays of 5-hydroxy indoleacetic acid (5HIAA).

CARCINOGENESIS, MUTAGENESIS, IMPAIRMENT OF FERTILITY

A two year study was performed in rats to evaluate the carcinogenic potential of naproxen at doses of 8 mg/kg/day, 16 mg/kg/day, and 24 mg/kg/day (50 mg/m^2, 100 mg/m^2, and 150 mg/m^2). The maximum dose used was 0.28 times the systemic exposure to humans at the recommended dose. No evidence of tumorigenicity was found.

PREGNANCY

Teratogenic Effects. Pregnancy Category C.

Reproduction studies have been performed in rats at 20mg/kg/day (125 mg/m^2/day, 0.23 times the human systemic exposure) rabbits at 20mg/kg/day (220 mg/m^2/day, 0.27 times the human systemic exposure) and mice at 170mg/kg/day (510 mg/m^2/day, 0.28 times the human systemic exposure) with no evidence of impaired fertility or harm to the fetus due to the drug. There are no adequate and well-controlled studies in pregnant women. Because animal reproduction studies are not always predicitve of human response, NAPRELAN® Tablets should be used during pregnancy only if the potential benefits justify the potential risks to the fetus.

Nonteratogenic effects

There is some evidence to suggest that when inhibitors of prostaglandin synthesis are used to delay preterm labor, there is an increased risk of neonatal complications such as necrotizing enterocolitis, patent ductus arteriosus and intracranial hemorrhage. Naproxen treatment given in late pregnancy to delay parturition has been associated with persistent pulmonary hypertension, renal dysfunction, and abnormal prostaglandin E levels in preterm infants. Because of the known effect of drugs of this class on the human fetal cardiovascular system (closure of the ductus arteriosus), use during third trimester should be avoided.

LABOR AND DELIVERY

In rat studies with NSAIDs, as with other drugs known to inhibit prostaglandin synthesis, an increased incidence of dystocia, delayed parturition, and decreased pup survival occurred. Naproxen-containing products are not recommended in labor and delivery because, through its prostaglandin synthesis inhibitory effect, naproxen may adversely affect fetal circulation and inhibit uterine contractions, thus increasing the risk of uterine hemorrhage. The effects of NAPRELAN® on labor and delivery in pregnant women are unknown.

NURSING MOTHERS

The naproxen anion has been found in the milk of lactating women at a concentration of approximately 1% of that found in the plasma. Because of the possible adverse effects of prostaglandin-inhibiting drugs on neonates, use in nursing mothers should be avoided.

PEDIATRIC USE

No pediatric studies have performed with NAPRELAN® Tablets, thus safety of NAPRELAN® Tablets in pediatric populations has not been established.

GERIATRIC USE

Clinical studies of NAPRELAN® Tablets did not include a sufficient number of subjects aged 65 and over to determine whether they respond differently from younger subjects. Other reported clinical experience has not identified differences in responses between the elderly and younger patients. In general, dose selection for the elderly patient should be cautious, usually starting at the low end of the dosing range, reflecting the greater frequency of decreased hepatic, renal, or cardiac function, and of concomitant disease or other drug therapy.

Aging may affect the pharmacokinetics of naproxen. Studies indicate that although total plasma concentration of naproxen is unchanged, the unbound plasma fraction of naproxen is increased in the elderly. Caution is advised when high doses are required and some adjustment of dosage may be required in elderly patients. Elderly or debilitated patients seem to tolerate GI ulcerations and bleeding less well than other individuals taking NSAIDs (see WARNINGS, RISK of GI Ulceration, Bleeding And Perforation With NSAID Therapy). Additionally, elderly patients may be more sensitive to dose-dependent reduction in renal prostaglandin formation while taking NSAIDs (see WARNINGS, Renal Effects).

ADVERSE REACTIONS

As with all drugs in this class, the frequency and severity of adverse events depends on several factors: the dose of the drug and duration of treatment; the age, the sex, physical condition of the patient; any concurrent medical diagnoses or individual risk factors. The following adverse reactions are divided into three parts based on frequency and whether or not the possibility exists of a causal relationship between drug usage and these adverse events. In those reactions listed as “Probable Causal Relationship” there is at least one case for each adverse reaction where there is evidence to suggest that there is a causal relationship between drug usage and the reported event. The adverse reactions reported were based on the results from two double-blind controlled clinical trials of three months duration with an additional nine month open-label extension. A total of 542 patients received NAPRELAN® Tablets either in the double-blind period or in the nine month open-label extension. Of these 542 patients, 232 received NAPRELAN® Tablets, 167 were initially treated with Naprosyn®*** and 143 were initially treated with placebo. Adverse reactions reported by patients who received NAPRELAN® Tablets are shown by body system. Those adverse reactions observed with naproxen but not reported in controlled trials with NAPRELAN® Tablets are italicized.

The most frequent adverse events from the double-blind and open-label clinical trials were headache (15%), followed by dyspepsia (14%), and flu syndrome (10%). The incidence of other adverse events occurring in 3% - 9% of the patients are marked with an asterisk.

Those reactions occurring in less than 3% of the patients are unmarked.

INCIDENCE GREATER THAN 1% (PROBABLE CAUSAL RELATIONSHIP)

Body as a Whole—Pain (back)*, pain*, infection*, fever, injury (accident), asthenia, pain chest, headache (15%), flu syndrome (10%).
Gastrointestinal—Nausea*, diarrhea*, constipation*, abdominal pain*, flatulence, gastritis, vomiting, dysphagia, dyspepsia (14%), heartburn*, stomatitis.
Hematologic—Anemia, ecchymosis.
Respiratory—Pharyngitis*, rhinitis*, sinusitis*, bronchitis, cough increased.
Renal—Urinary tract infection*, cystitis.
Dermatologic—Skin rash*, skin eruptions*, ecchymoses*, purpura.
Metabolic and Nutrition—Peripheral edema, hyperglycemia.
Central Nervous System—Dizziness, paresthesia, insomnia, drowsiness*, lightheadedness.
Cardiovascular—Hypertension, edema*, dyspnea*, palpitations.
Musculoskeletal—Cramps (leg), myalgia, arthralgia, joint disorder, tendon disorder.
Special Senses—Tinnitus*, hearing disturbances, visual disturbances.
General—Thirst.

INCIDENCE LESS THAN 1% (PROBABLE CAUSAL RELATIONSHIP)

Body as a Whole—Abscess, monilia, neck rigid, pain neck, abdomen enlarged, carcinoma, cellulitis, edema general, LE syndrome, malaise, mucous membrane disorder, allergic reaction, pain pelvic.
Gastrointestinal—Anorexia, cholecystitis, cholelithiasis, eructation, GI hemorrhage, rectal hemorrhage, stomatitis aphthous, stomatitis ulcer, ulcer mouth, ulcer stomach, periodontal abscess, cardiospasm, colitis, esophagitis, gastroenteritis, GI disorder, rectal disorder, tooth disorder, hepatosplenomegaly, liver function abnormality, melena, ulcer esophagus, hematemesis, jaundice, pancreatitis, necrosis.
Renal—Dysmenorrhea, dysuria, kidney function abnormality, nocturia, prostate disorder, pyelonephritis, carcinoma breast, urinary incontinence, kidney calculus, kidney failure, menorrhagia, metrorrhagia, neoplasm breast, nephrosclerosis, hematuria, pain kidney, pyuria, urine abnormal, urinary frequency, urinary retention, uterine spasm, vaginitis, glomerular nephritis, hyperkalemia, interstitial nephritis, nephrotic syndrome, renal disease, renal failure, renal papillary necrosis.
Hematologic—Leukopenia, bleeding time increased, eosinophilia, abnormal RBC, abnormal WBC, thrombocytopenia, agranulocytosis, granulocytopenia.
Central Nervous System—Depression, anxiety, hypertonia, nervousness, neuralgia, neuritis, vertigo, amnesia, confusion, co-ordination, abnormal diplopia, emotional lability, hematoma subdural, paralysis, dream abnormalities, inability to concentrate, muscle weakness.
Dermatologic: Angiodermatitis, herpes simplex, dry skin, sweating, ulcer skin, acne, alopecia, dermatitis contact, eczema, herpes zoster, nail disorder, skin necrosis, subcutaneous nodule, pruritus, urticaria, neoplasm skin, photosensitive dermatitis, photosensitivity reactions resembling porphyria cutaneous tarda, epidermolysis bullosa.
Special Senses—Amblyopia, scleritis, cataract, conjunctivitis, deaf, ear disorder, keratoconjunctivitis, lacrimation disorder, otitis media, pain eye.
Cardiovascular—Angina pectoris, coronary artery disease, myocardial infarction, deep thrombophlebitis, vasodilation, vascular anomaly, arrhythmia, bundle branch block, abnormal ECG, heart failure right, hemorrhage, migraine, aortic stenosis, syncope, tachycardia, congestive heart failure.
Respiratory—Asthma, dyspnea, lung edema, laryngitis, lung disorder, epistaxis, pneumonia, respiratory distress, respiratory disorder, eosinophilic pneumonitis.
Musculoskeletal—Myasthenia, bone disorder, spontaneous bone fracture, fibrotendinitis, bone pain, ptosis, spasm general, bursitis.
Metabolic and Nutrition—Creatinine increase, glucosuria, hypercholesteremia, albuminuria, alkalosis, BUN increased, dehydration, edema, glucose tolerance decrease, hyperuricemia, hypokalemia, SGOT increase, SGPT increase, weight decrease.
General—Anaphylactoid reactions, angioneurotic edema, menstrual disorders, hypoglycemia, pyrexia (chills and fevers).

INCIDENCE LESS THAN 1% (CAUSAL RELATIONSHIP UNKNOWN)

Other adverse reactions listed in the naproxen package label, but not reported by those who received NAPRELAN® Tablets are shown in italics. These observations are being listed as alerting information to the physician.

Hematologic—Aplastic anemia, hemolytic anemia.
Central Nervous System—Aseptic meningitis, cognitive dysfunction.
Dermatologic—Epidermal necrolysis, erythema multiforme, Stevens-Johnson syndrome.
Gastrointestinal—Non-peptic GI ulceration, ulcerative stomatitis.
Cardiovascular—Vasculitis.

OVERDOSAGE

Significant naproxen overdosage may be characterized by drowsiness, heartburn, indigestion, nausea or vomiting. Because naproxen sodium may be rapidly absorbed, high and early blood levels should be anticipated. A few patients have experienced seizures, but it is not clear whether or not these were drug-related. It is not known what dose of the drug would be life threatening. The oral LD50 of the drug is 500 mg/kg in rats, 1200 mg/kg in mice, 4000 mg/kg in hamsters and greater than 1000 mg/kg in dogs. In animals 0.5 g/kg of activated charcoal was effective in reducing plasma levels of naproxen.

Patients should be managed by symptomatic and supportive care following an NSAID overdose. There are no specific antidotes. Hemodialysis does not decrease the plasma concentration of naproxen because of the high degree of its protein binding. Emesis and/or activated charcoal (60 to 100 g in adults, 1 to 2 g/kg in children) and/or osmotic carthartic may be indicated in patients seen within 4 hours of ingestion with symptoms or following a large overdose. Forced diuresis, alkalinization of urine or hemoperfusion may not be useful due to high protein binding.

DOSAGE AND ADMINISTRATION

Carefully consider the potential benefits and risks of NAPRELAN® and other treatment options before deciding to use NAPRELAN®. Use the lowest effective dose for the shortest duration consistent with individual patient treatment goals (see WARNINGS).

After observing the response to initial therapy with NAPRELAN®, the dose and frequency should be adjusted to suit an individual patient's needs.

For the relief of:

Rheumatoid Arthritis, Osteoarthritis, and Ankylosing Spondylitis

The recommended starting dose of NAPRELAN® Tablets in adults is two NAPRELAN® 375 mg tablets (750 mg) once daily, one NAPRELAN® 750 mg (750 mg) once daily, or two NAPRELAN® 500 mg tablets (1000 mg) once a daily. Patients already taking naproxen 250 mg, 375 mg, or 500mg twice daily (morning and evening) may have their total daily dose replaced with NAPRELAN® Tablets as a single daily dose.

During long-term administration, the dose of NAPRELAN® Tablets may be adjusted up or down depending on the clinical response of the patient. In patients who tolerate lower doses of NAPRELAN® Tablets well, the dose may be increased to two NAPRELAN® 750 mg tablets (1500 mg), or three NAPRELAN® 500 mg tablets (1500 mg) once daily for limited periods when a higher level of anti-inflammatory/analgesic activity is required. When treating patients, especially at the higher dose levels, the physician should observe sufficient increased clinical benefit to offset the potential increased risk (see CLINICAL PHARMACOLOGY). The lowest effective dose should be sought and used in every patient. Symptomatic improvement in arthritis usually begins within one week; however, treatment for two weeks may be required to achieve a therapeutic benefit.

A lower dose should be considered in patients with renal or hepatic impairment or in elderly patients (see PRECAUTIONS). Studies indicate that although total plasma contcentration of naproxen is unchanged, the unbound plasma fraction of naproxen is increased in the elderly. Caution is advised when high doses are required and some adjustment of dosage may be required in elderly patients. As with other drugs used in the elderly it is prudent to use the lowest effective dose.

Management of Pain, Primary Dysmenorrhea, and Acute Tendinitis and Bursitis

The recommended starting dose is two NAPRELAN® 500 mg tablets (1000 mg) once daily. For patients requiring greater analgesic benefit, two NAPRELAN® 750 mg tablets (1500 mg) or three NAPRELAN® 500 mg tablets (1500 mg) may be used for a limited period. Thereafter, the total daily dose should not exceed two NAPRELAN® 500 mg tablets (1000 mg). The NAPRELAN® DOSE CARD provides a 10 day tapered dose regimen contained in a single blister dose pack that provides 1500 mg given once daily (two NAPRELAN® 750 mg tablets) for 3 days, with a taper to 1000 mg given once daily (two NAPRELAN® 500 mg tablets) for the remaining 7 days.

Acute Gout

The recommended dose on the first day is two to three NAPRELAN® 500 mg tablets (1000 - 1500 mg) once daily, followed by two NAPRELAN® 500 mg tablets (1000 mg) once daily, until the attack has subsided.

HOW SUPPLIED

NAPRELAN® (naproxen sodium) Controlled-Release Tablets are available as follows:

NAPRELAN® 375: white, capsule-shaped tablet with “N” on one side and “375” on the reverse; in bottles of 60; NDC 21695-905-60. Each tablet contains 412.5 mg naproxen sodium equivalent to 375 mg naproxen.
NAPRELAN® 500: white, capsule-shaped tablet with “N” on one side and “500” on the reverse; in bottles of 75; NDC 21695-906-60. Each tablet contains 550 mg naproxen sodium equivalent to 500 mg naproxen.

Rx Only

US Patent 5,637,320

Store at controlled room temperature, 20° - 25° C (68° - 77° F).

Dispense in a well-closed container.

______________________________________________________________

* Registered Trademark of Elan Corporation plc

** Registered Trademark of Elan Pharma Int. Ltd.

*** Naprosyn® is a registered trademark of Syntex Puerto Rico, Inc.

Manufactured for: Victory Pharma, Inc., San Diego, CA 92130

Manufactured by: Elan Pharma International Ltd., Athlone, Ireland

PI3750107

Rev 8/09

MEDICATION GUIDE

Medication Guide for Non-Steroidal Anti-Inflammatory Drugs (NSAIDs)

(See the end of this Medication Guide for a list of prescription NSAID medicines.)

NAPRELAN®
(naproxen sodium)
CONTROLLED-RELEASE TABLETS

What is the most important information I should know about medicines called Non-Steroidal Anti-Inflammatory Drugs (NSAIDs)?

NSAID medicines may increase the chance of a heart attack or stroke that can lead to death._

This chance increases:

- with longer use of NSAID medicines
- in people who have heart disease

NSAID medicines should never be used right before or after a heart surgery called a “coronary artery bypass graft (CABG).”

NSAID medicines can cause ulcers and bleeding in the stomach and intestines at any time during treatment. Ulcers and bleeding:

- can happen without warning symptoms
- may cause death

The chance of a person getting an ulcer or bleeding increases with:

- taking medicines called “corticosteroids” and “anti-coagulants”
- longer use
- smoking
- drinking alcohol
- older age
- having poor health

NSAID medicines should only be used:

- exactly as prescribed
- at the lowest dose possible for your treatment
- for the shortest time needed

________________________________________________

What are Non-Steroidal Anti-Inflammatory Drugs (NSAIDs)?

NSAID medicines are used to treat pain and redness, swelling, and heat (inflammation) from medical conditions such as:

- different types of arthritis
- menstrual cramps and other types of short-term pain

Who should not take a Non-Steroidal Anti-Inflammatory Drug (NSAID)?

Do not take an NSAID medicine:

- if you had an asthma attack, hives, or other allergic reaction with aspirin or any other NSAID medicine.
- for pain right before or after heart bypass surgery.

Tell your healthcare provider:

- about all your medical conditions
- about all of the medicines you take. NSAIDs and some other medicines can interact with each other and cause serious side effects. Keep a list of your medicines to show to your healthcare provider and pharmacist.
- if you are pregnant. NSAID medicines should not be used by pregnant women late in their pregnancy.
- if you are breastfeeding. Talk to your doctor.

What are the possible side effects of Non-Steroidal Anti-Inflammatory Drugs (NSAIDs)?

Serious side effects include:

- heart attack
- stroke
- high blood pressure
- heart failure from body swelling (fluid retention)
- kidney problems including kidney failure
- bleeding and ulcers in the stomach and intestine
- low red blood cells (anemia)
- life-threatening skin reactions
- life-threatening allergic reactions
- liver problems including liver failure
- asthma attacks in people who have asthma

Other side effects include:

- stomach pain
- constipation
- diarrhea
- gas
- heartburn
- nausea
- vomiting
- dizziness

Get emergency help right away if you have any of the following symptoms:

- shortness of breath or trouble breathing
- chest pain
- weakness in one part or side of your body
- slurred speach
- swelling of the face or throat

Stop your NSAID medicine and call your healthcare provider right away if you have any of the following symptoms:

- nausea
- more tired or weaker than usual
- itching
- your skin or eyes look yellow
- stomach pain
- flu-like symptoms
- vomit blood
- there is blood in your bowel movement or it is black and sticky like tar
- unusual weight gain
- skin rash or blisters with fever
- swelling of the arms and legs, hands and feet

These are not all the side effects with NSAID medicines. Talk to your healthcare provider or pharmacist for more information about NSAID medicines. Call your doctor for medial advice about side effects. You may report side effects to FDA at 1-800-FDA-1088.

Other information about Non-Steroidal Anti-Inflammatory Drugs (NSAIDs)

- Aspirin is an NSAID medicine but it does not increase the chance of a heart attack. Aspirin can cause bleeding in the brain, stomach, and intestines. Aspirin can also cause ulcers in the stomach and intestines.
- Some of these NSAID medicines are sold in lower doses without a prescription (over-the-counter). Talk to your healthcare provider before using over-the-counter NSAIDs for more than 10 days.

NSAID medicines that need a prescription
Generic Name | Tradename
Celecoxib | Celebrex
Diclofenac | Cataflam, Voltaren, Arthrotec (combined with misoprostol)
Diflunisal | Dolobid
Etodolac | Lodine, Lodine XL
Fenoprofen | Nalfon, Nalfon 200
Flurbiprofen | Ansaid
Ibuprofen | Motrin, Tab-Profen, Vicoprofen* (combined with hydrocodone), Combunox (combined with oxycodone)
Indomethacin | Indocin, Indocin SR, Indo-Lemmon, Indomethagan
Ketoprofen | Oruvail
Ketorolac | Toradol
Mefenamic Acid | Ponstel
Meloxicam | Mobic
Nabumetone | Relafen
Naproxen | Naprosyn, Anaprox, Anaprox DS, EC-Naproxyn, NAPRELAN, Naprapac (copackaged with lansoprazole)
Oxaprozin | Daypro
Piroxicam | Feldene
Sulindac | Clinoril
Tolmetin | Tolectin, Tolectin DS, Tolectin 600
*Vicoprofen contains the same dose of ibuprofen as over-the-counter (OTC) NSAIDs, and is usually used for less than 10 days to treat pain. The OTC NSAID label warns that long term continuous use may increase the risk of heart attack or stroke.

This Medication Guide has been approved by the U.S. Food and Drug Administration.

Repackaged by:

Rebel Distributors Corp

Thousand Oaks, CA 91320